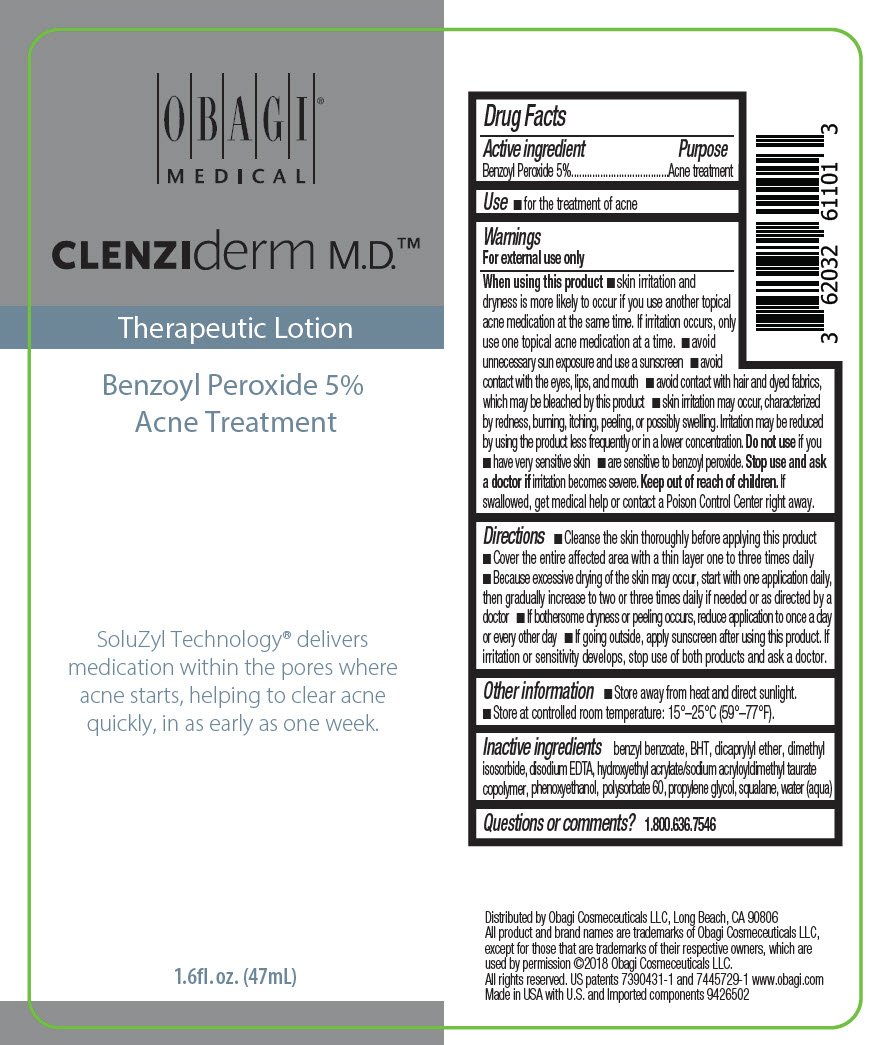 DRUG LABEL: CLENZIDERM THERAPEUTIC
NDC: 62032-611 | Form: LOTION
Manufacturer: Obagi Cosmeceuticals LLC
Category: otc | Type: HUMAN OTC DRUG LABEL
Date: 20250101

ACTIVE INGREDIENTS: BENZOYL PEROXIDE 50 mg/1 mL
INACTIVE INGREDIENTS: BENZYL BENZOATE; DICAPRYLYL ETHER; PROPYLENE GLYCOL; HYDROXYETHYL ACRYLATE/SODIUM ACRYLOYLDIMETHYL TAURATE COPOLYMER (100000 MPA.S AT 1.5%); SQUALANE; POLYSORBATE 60; DIMETHYL ISOSORBIDE; PHENOXYETHANOL; EDETATE DISODIUM; BUTYLATED HYDROXYTOLUENE; WATER

CLENZIDERM THERAPEUTIC LOTION

Drug Facts

Active ingredient

Benzoyl Peroxide 5%

Purpose

Acne treatment

Use

- for the treatment of acne

Warnings

For external use only

When using this product

- skin irritation and dryness is more likely to occur if you use another topical acne medication at the same time. If irritation occurs, only use one topical acne medication at a time.
- avoid unnecessary sun exposure and use a sunscreen
- avoid contact with the eyes, lips, and mouth
- avoid contact with hair and dyed fabrics, which may be bleached by this product
- skin irritation may occur, characterized by redness, burning, itching, peeling, or possibly swelling. Irritation may be reduced by using the product less frequently or in a lower concentration.

Do not use if you

- have very sensitive skin
- are sensitive to benzoyl peroxide.

Stop use and ask a doctor if irritation becomes severe.

Keep out of reach of children. If swallowed, get medical help or contact a Poison Control Center right away.

Directions

- Cleanse the skin thoroughly before applying this product
- Cover the entire affected area with a thin layer one to three times daily
- Because excessive drying of the skin may occur, start with one application daily, then gradually increase to two or three times daily if needed or as directed by a doctor
- If bothersome dryness or peeling occurs, reduce application to once a day or every other day
- If going outside, apply sunscreen after using this product. If irritation or sensitivity develops, stop use of both products and ask a doctor.

Other information

- Store away from heat and direct sunlight.
- Store at controlled room temperature: 15°–25°C (59°–77°F).

Inactive ingredients

benzyl benzoate, BHT, dicaprylyl ether, dimethyl isosorbide, disodium EDTA, hydroxyethyl acrylate/sodium acryloyldimethyl taurate copolymer, phenoxyethanol, polysorbate 60, propylene glycol, squalane, water (aqua)

Questions or comments?

1.800.636.7546

Distributed by Obagi Cosmeceuticals LLC, Long Beach, CA 90806

PRINCIPAL DISPLAY PANEL - 47 mL Bottle Label

OBAGI®
MEDICAL

CLENZIderm M.D.™

Therapeutic Lotion

Benzoyl Peroxide 5%
Acne Treatment

SoluZyl Technology® delivers
medication within the pores where
acne starts, helping to clear acne
quickly, in as early as one week.

1.6fl. oz. (47mL)